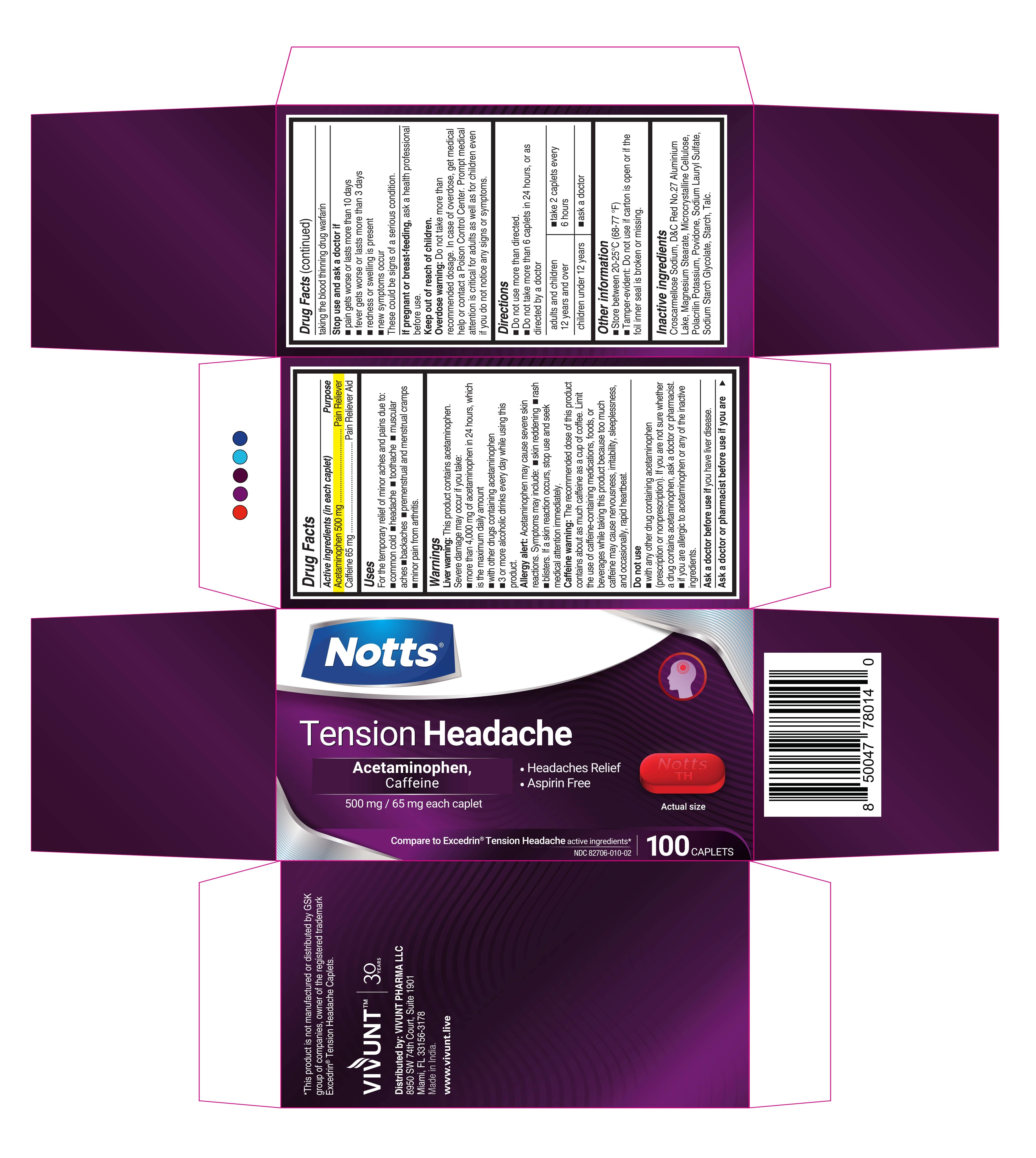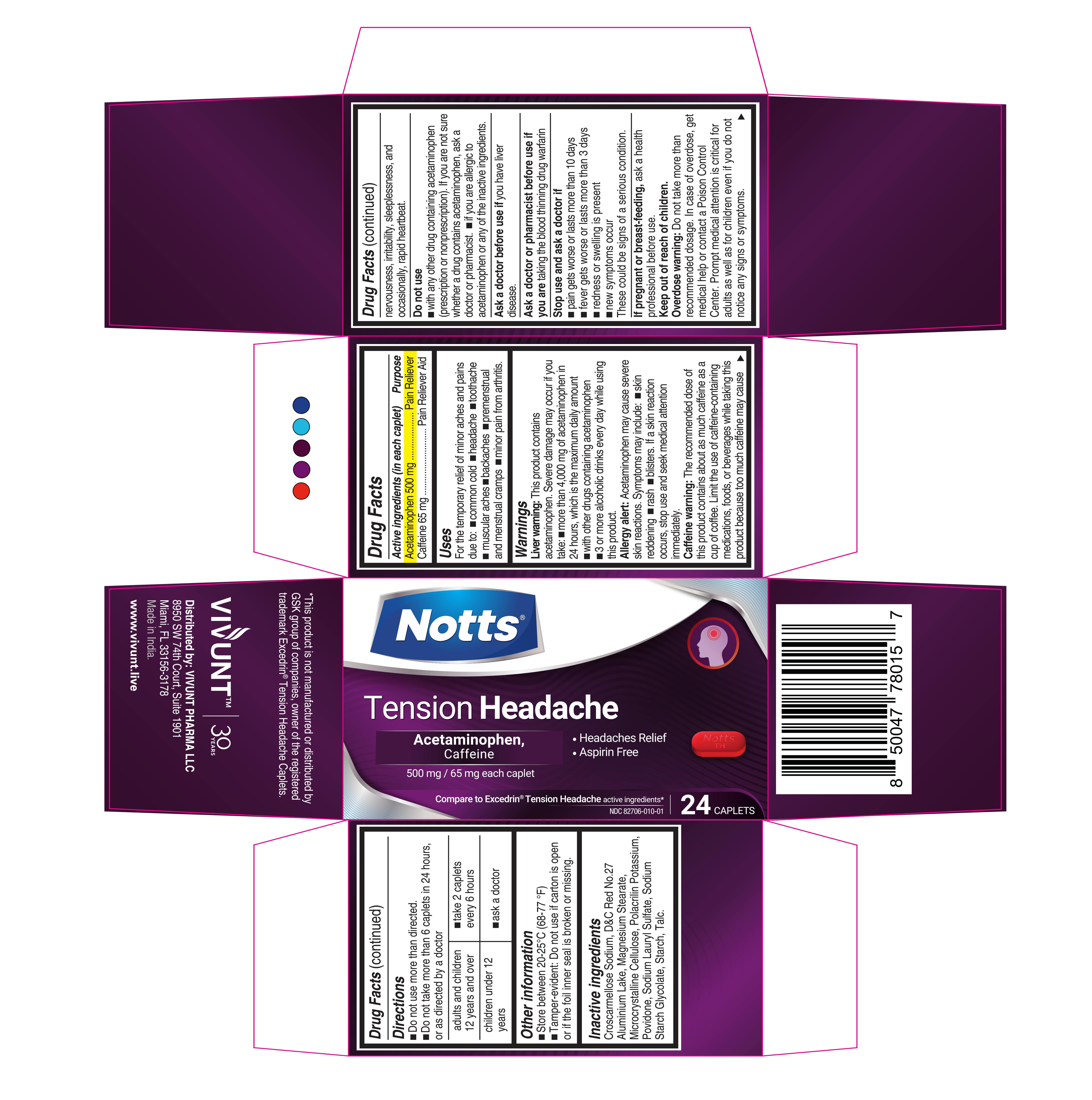 DRUG LABEL: NOTTS - Tension Headache
NDC: 82706-010 | Form: TABLET
Manufacturer: VIVUNT PHARMA LLC
Category: otc | Type: HUMAN OTC DRUG LABEL
Date: 20231124

ACTIVE INGREDIENTS: ACETAMINOPHEN 500 mg/1 1; CAFFEINE 65 mg/1 1
INACTIVE INGREDIENTS: TALC; D&C RED NO. 27 ALUMINUM LAKE; SODIUM STARCH GLYCOLATE TYPE A; STARCH, CORN; MAGNESIUM STEARATE; MICROCRYSTALLINE CELLULOSE; SODIUM LAURYL SULFATE; POVIDONE; CROSCARMELLOSE SODIUM; POLACRILIN POTASSIUM

NOTTS - Tension Headache

ACTIVE INGREDIENT

Active ingredients (in each caplet) | Purpose
Acetaminophen 500 mg | Pain Reliever
Caffeine 65 mg | Pain reliever Aid

Uses

For the temporary relief of minor aches and pains due to:

- common cold
- headache
- toothache
- muscular aches
- backaches
- premenstrual and menstrual cramps
- minor pain from arthritis

Warnings

Liver Warning:

Liver warning: This product contains acetaminophen.

Severe damage may occur if you take:

- more than 4,000 mg of acetaminophen in 24 hours, which is the maximum daily amount
- with other drugs containing acetaminophen
- 3 or more alcoholic drinks every day ehile using this product.

Allergy alert:

Acetaminophen may cause severe sking reactions. Symptoms may include:

- skin reddening
- rash
- blisters.

If a skin reactions occurs, stop use and seek medical attention immediately

Caffeine warning:

The recommended dose of this product contains about as much caffeine as a cup of coffee. Limit the use of caffeine-containing medications, foods, or beverages while taking this product because too much caffeine may cause nervousness, irritability, sleeplessness. and occasionally, rapid heartbeat.

Do not use

- with any other drug containing acetaminophen (prescription or nonprescription). If you are not sure whether a drug contains acetaminophen, ask a doctor or pharmacist.
- if you are allergic to acetaminophen or any of the inactive ingredients.

Ask a doctor before use if

you have liver disease.

Ask a doctor or pharmacist before use if you are

taking the blood thinning drug warfarin

Stop use and ask a doctor if

- pain gets worse or lasts more than 10 days
- fever gets worse or lasts more than 3 days
- redness or swelling is present
- new symptoms occur

These could be signs of a serious condition

If pregnant or breast-feeding,

ask a healt professional before use.

Overdose warning:

Do not take more than recommended dosage. In case of overdose, get medical help or contact a Poison Control Center. Prompt medical attention is critical for adults as well as for children even if you do not notice any signs or symptoms.

Directions

- Do not use more than directed
- Do not take more than 6 caplets in 24 hours, or as directed by a doctor

adults and children 12 years and over | - take 2 caplets every 6 hours
children under 12 years | - ask a doctor

Other information

- Store between 20-25 °C (68-77 °F)
- Tamper-evident: Do not use if carton is open or the foil inner seal is broken or missing.

Inactive ingredients

Croscarmellose Sodium, D&C Red No.27 Aluminium Lake, Magnesium Stearate, Microcrystalline Cellulose, Polacrilin Potassium, Povidone, Sodium Lauryl Sulfate, Sodium Starch Glycolate, Starch, Talc.

*This product is not manufactured or distributed by GSK group of companies, owner of the registered trademark Excedrin® Tension Headache Caplets.

Distributed by: VIVUNT PHARMA LLC

8950 SW 74th Court, Suite 1901

Miami, FL 33156-3178

Made in India.

www.vivunt.live

Package Principal Display Panel - TH 24 Caplets

NOTTS®

Tension Headache

500 mg 65 mg each caplet

- Headaches Relief
- Aspirin Free

Compare to Excedrin® Tension Headache active ingredients*

NDC 82706-010-01

24 CAPLETS

Package Principal Display Panel - TH 100 Caplets

NOTTS®

Tension Headache

500 mg 65 mg each caplet

Headaches Relief
Aspirin Free

Compare to Excedrin® Tension Headache active ingredients*

NDC 82706-010-02

100 CAPLETS